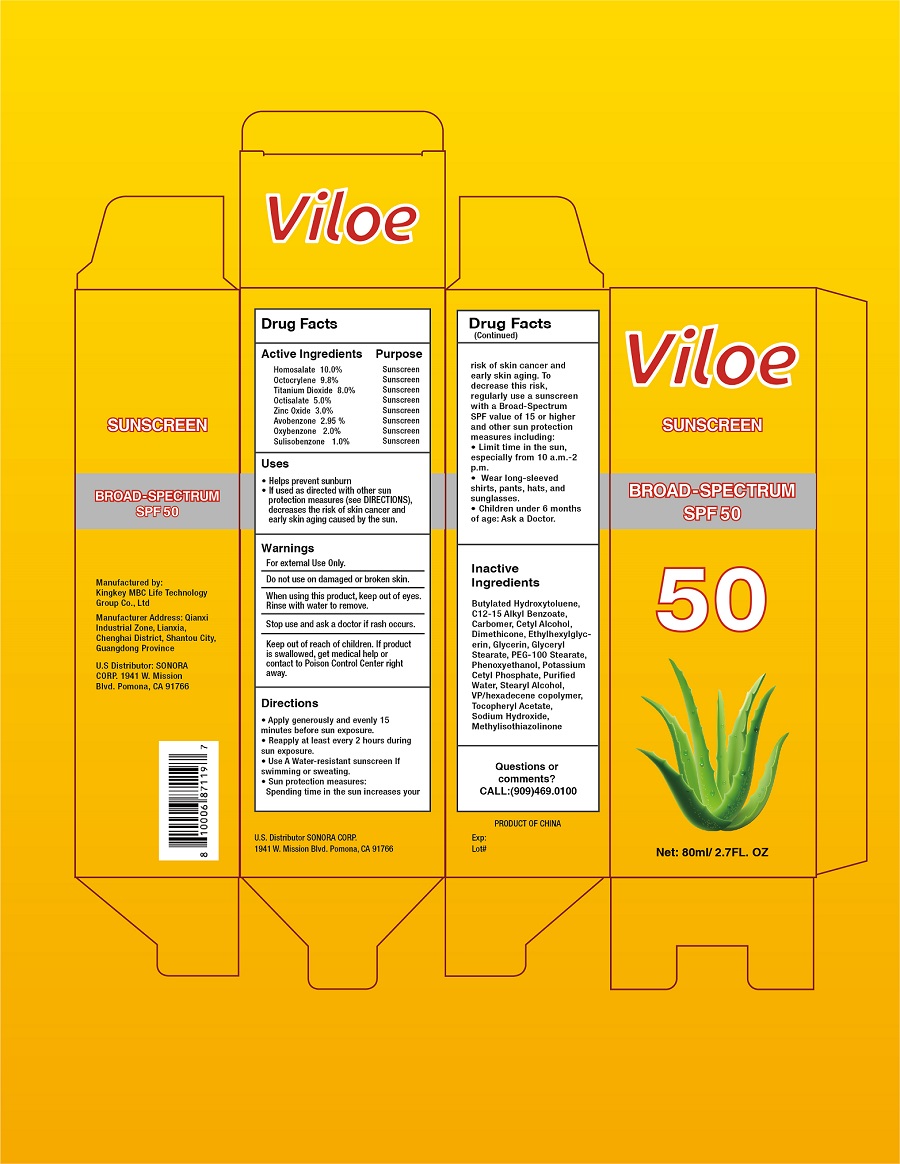 DRUG LABEL: SPF50 Sunscreen
NDC: 73928-010 | Form: CREAM
Manufacturer: KINGKEY MBC LIFE TECHNOLOGY GROUP CO., LTD
Category: otc | Type: HUMAN OTC DRUG LABEL
Date: 20251007

ACTIVE INGREDIENTS: TITANIUM DIOXIDE 8 g/100 mL; ZINC OXIDE 3 g/100 mL; HOMOSALATE 10 g/100 mL; OCTOCRYLENE 9.8 g/100 mL; OXYBENZONE 2 g/100 mL
INACTIVE INGREDIENTS: WATER

PACKAGE LABEL

80ml in 1 TUBE NDC: 73928-010-01